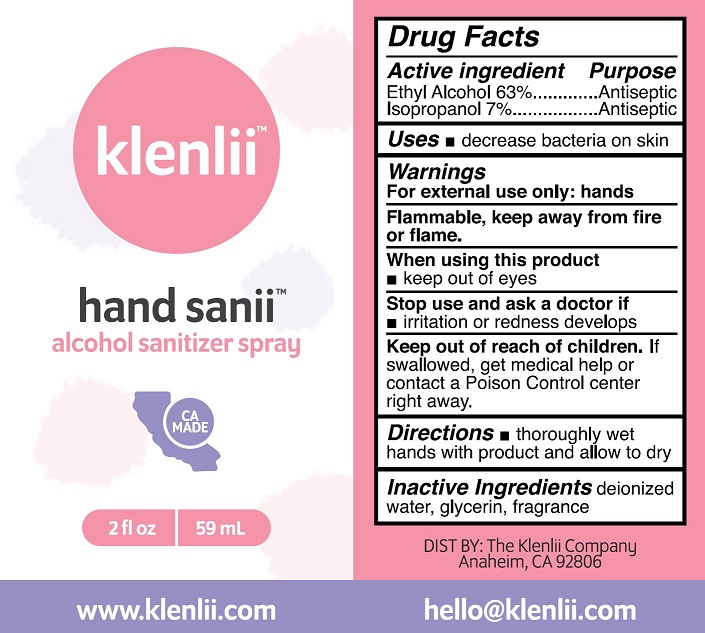 DRUG LABEL: KLENLII HAND SANII ALCOHOL SANITIZER
NDC: 78016-107 | Form: SPRAY
Manufacturer: Klenlii Company
Category: otc | Type: HUMAN OTC DRUG LABEL
Date: 20240509

ACTIVE INGREDIENTS: ALCOHOL 63 mL/100 mL; ISOPROPYL ALCOHOL 7 mL/100 mL
INACTIVE INGREDIENTS: WATER; GLYCERIN

KLENLII HAND SANII ALCOHOL SANITIZER SPRAY (63% ETHYL ALCOHOL, 7% IPA) (78016-107)

ACTIVE INGREDIENT

ETHYL ALCOHOL 63%

ISOPROPYL ALCOHOL 7%

PURPOSE

ANTISEPTIC

USES

- DECREASE BACTERIA ON SKIN

WARNINGS

FOR EXTERNAL USE ONLY: HANDS

FLAMMABLE, KEEP AWAY FROM FIRE OR FLAME.

WHEN USING THIS PRODUCT

- KEEP OUT OF EYES

STOP USE AND ASK DOCTOR IF

- IRRITATION OR REDNESS DEVELOPS

KEEP OUT OF REACH OF CHILDREN. IF SWALLOWED, GET MEDICAL HELP OR CONTACT A POISON CONTROL CENTER RIGHT AWAY.

DIRECTIONS

- THOROUGHLY WET HANDS WITH PRODUCT AND ALLOW TO DRY

INACTIVE INGREDIENTS

DEIONIZED WATER, GLYCERIN